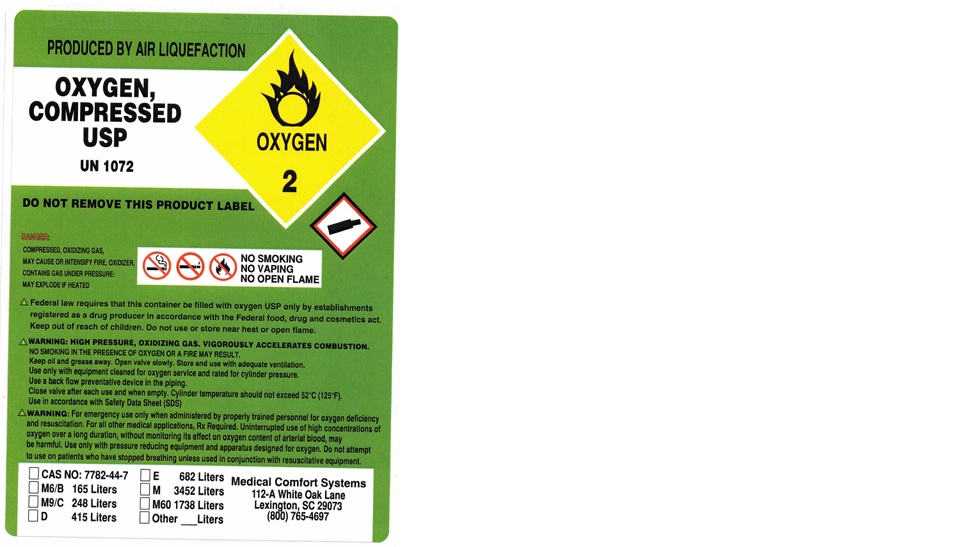 DRUG LABEL: Oxygen
NDC: 66365-001 | Form: GAS
Manufacturer: Medical Comfort Systems Inc
Category: prescription | Type: HUMAN PRESCRIPTION DRUG LABEL
Date: 20251008

ACTIVE INGREDIENTS: OXYGEN 998 mL/1 L

Oxygen

PACKAGE LABEL

PRODUCED BY AIR LIQUEFACTION

OXYGEN, COMPRESSED USP

UN 1072

DO NOT REMOVE THIS PRODUCT LABEL

DANGER:

COMPRESSED, OXIDIZING GAS, MAY CAUSE OR INTENSIFY FIRE, OXIDIZER, CONTAINS GAS UNDER PRESSURE: MAY EXPLODE IF HEATED

NO SMOKING

NO VAPING

NO OPEN FLAME

Federal law requires that this container be filled with oxygen USP only by establishments registered as a drug producer in accordance with the Federal food, drug and cosmetics act. Keep out of reach of children. Do not use or store near heat or open flame.

WARNING: HIGH PRESSURE, OXIDIZING GAS. VIGOROUSLY ACCELERATES COMBUSTION.

NO SMOKING IN THE PRESENCE OF OXYGEN OR A FIRE MAY RESULT.

Keep oil and grease away. Open valve slowly. Store and use with adequate pressure.

Use only with equipment cleaned for oxygen service and rated for cylinder pressure.

Use a back flow preventive device in the piping.

Close valve after each use and when empty. Cylinder temperature should not exceed 52 C (125 F).

Use in accordance with Safety Data Sheet (SDS)

WARNING: For emergency use only when administered by properly trained personnel for oxygen deficiency and resuscitation. For all other medical application, Rx Required. Uninterrupted use of high concentrations of oxygen over a long duration, without monitoring its effect on oxygen content of arterial blood, may be harmful. Use only with pressure reducing equipment and apparatus designed for oxygen. Do not attempt to use on patients who have stopped breathing unless used in conjunction with resuscitative equipment.

CAS NO: 7782-7 E 682 Liters

M6/B 165 Liters M 3458 Liters

M9/C 248 Liters M60 1738 Liters

D 415 Liters Other Liters

Medical Comfort Systems

112-A White Oak Lane

Lexington, SC 29073

(800) 765-4697